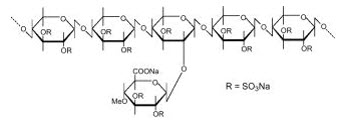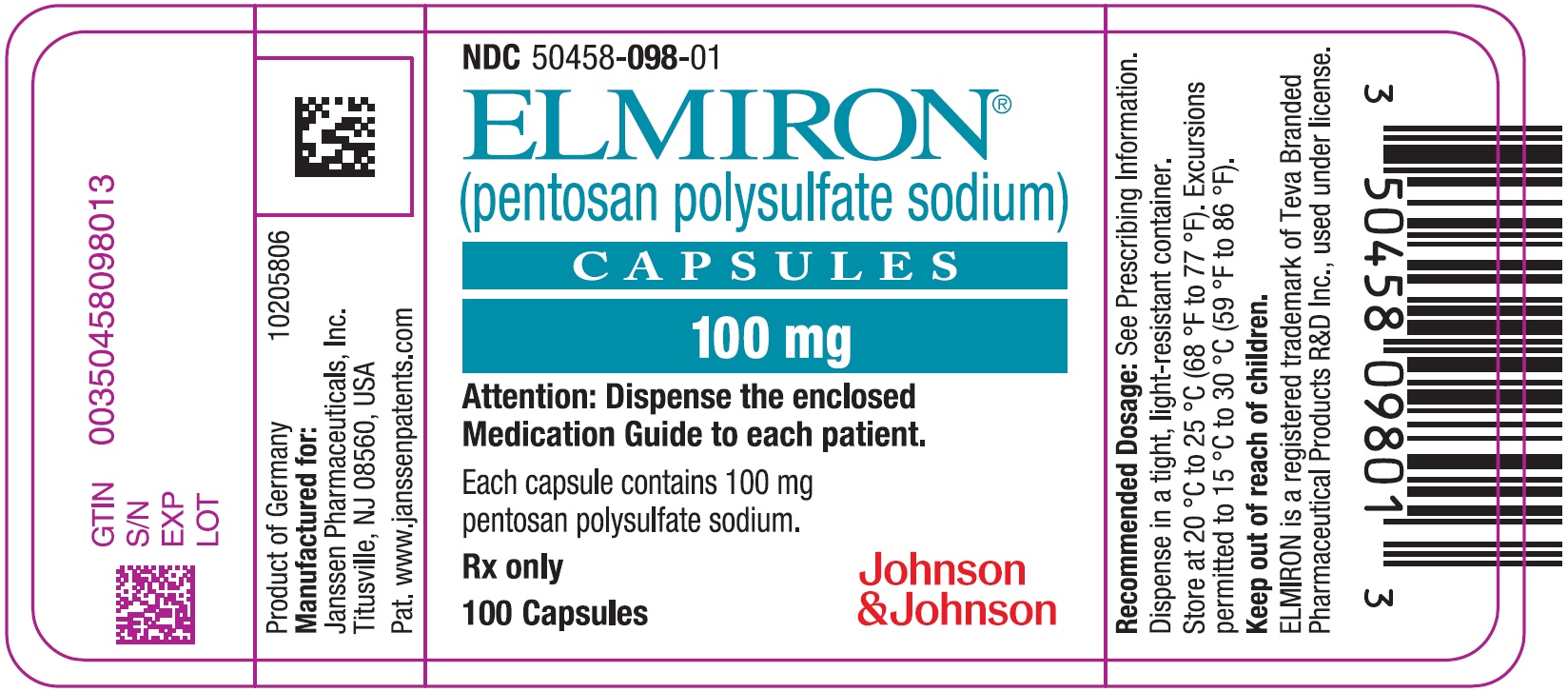 DRUG LABEL: ELMIRON
NDC: 50458-098 | Form: CAPSULE, GELATIN COATED
Manufacturer: Janssen Pharmaceuticals, Inc.
Category: prescription | Type: HUMAN PRESCRIPTION DRUG LABEL
Date: 20240918

ACTIVE INGREDIENTS: PENTOSAN POLYSULFATE SODIUM 100 mg/1 1
INACTIVE INGREDIENTS: MICROCRYSTALLINE CELLULOSE; MAGNESIUM STEARATE; FERROSOFERRIC OXIDE; FD&C BLUE NO. 2; ALUMINUM OXIDE; FD&C RED NO. 40; FD&C BLUE NO. 1; D&C YELLOW NO. 10; BUTYL ALCOHOL; PROPYLENE GLYCOL; TITANIUM DIOXIDE

ELMIRON®100 MG
(PENTOSAN POLYSULFATE SODIUM)
CAPSULES

PRESCRIBING INFORMATION

DESCRIPTION

Pentosan polysulfate sodium is a semi-synthetically produced heparin-like macromolecular carbohydrate derivative, which chemically and structurally resembles glycosaminoglycans. It is a white odorless powder, slightly hygroscopic and soluble in water to 50% at pH 6. It has a molecular weight of 4000 to 6000 Dalton with the following structural formula:

ELMIRON®is supplied in white, opaque hard gelatin capsules containing 100 mg pentosan polysulfate sodium, microcrystalline cellulose, and magnesium stearate. It also contains pharmaceutical glaze (modified) in SD-45, synthetic black iron oxide, FD&C Blue No. 2 aluminum lake, FD&C Red No. 40 aluminum lake, FD&C Blue No. 1 aluminum lake, D&C Yellow No. 10 aluminum lake, n-butyl alcohol, propylene glycol, SDA-3A alcohol, and titanium dioxide. It is formulated for oral use.

CLINICAL PHARMACOLOGY

General

Pentosan polysulfate sodium is a low molecular weight heparin-like compound. It has anticoagulant and fibrinolytic effects. The mechanism of action of pentosan polysulfate sodium in interstitial cystitis is not known.

Pharmacokinetics

Absorption

In a clinical pharmacology study in which healthy female volunteers received a single oral 300 or 450 mg dose of pentosan polysulfate sodium containing radiolabeled drug as a solution under fasted conditions, maximal levels of plasma radioactivity were seen approximately at a median of 2 hours (range 0.6-120 hours) after dosing. Based on urinary excretion of radioactivity, a mean of approximately 6% of a radiolabeled oral dose of pentosan polysulfate sodium is absorbed and reaches the systemic circulation.

Food Effects: In clinical trials, ELMIRON®was administered with water 1 hour before or 2 hours after meals; the effect of food on absorption of pentosan polysulfate sodium is not known.

Distribution

Preclinical studies with parenterally administered radiolabeled pentosan polysulfate sodium showed distribution to the uroepithelium of the genitourinary tract with lesser amounts found in the liver, spleen, lung, skin, periosteum, and bone marrow. Erythrocyte penetration is low in animals.

Metabolism

The fraction of pentosan polysulfate sodium that is absorbed is metabolized by partial desulfation in the liver and spleen, and by partial depolymerization in the kidney to a large number of metabolites. Both the desulfation and depolymerization can be saturated with continued dosing.

Excretion

Following administration of an oral solution of a 300 or 450 mg dose of pentosan polysulfate sodium containing radiolabeled drug to groups of healthy subjects, plasma radioactivity declined with mean half-lives of 27 and 20 hours, respectively. A large proportion of the orally administered dose of pentosan polysulfate sodium (mean 84% in the 300 mg group and 58% in the 450 mg group) is excreted in feces as unchanged drug. A mean of 6% of an oral dose is excreted in the urine, mostly as desulfated and depolymerized metabolites. Only a small fraction of the administered dose (mean 0.14%) is recovered as intact drug in urine.

Special Populations

The pharmacokinetics of pentosan polysulfate sodium has not been studied in geriatric patients or in patients with hepatic or renal impairment. See also PRECAUTIONS-Hepatic Insufficiency.

Drug-Drug Interactions

In a study in which healthy subjects received pentosan polysulfate sodium 100 mg capsule or placebo every 8 hours for 7 days, and were titrated with warfarin to an INR of 1.4 to 1.8, the pharmacokinetic parameters of R-warfarin and S-warfarin were similar in the absence and presence of pentosan polysulfate sodium. INR for warfarin + placebo and warfarin + pentosan polysulfate sodium were comparable. See also PRECAUTIONSon the use of ELMIRON®in patients receiving other therapies with anticoagulant effects.

Pharmacodynamics

The mechanism by which pentosan polysulfate sodium achieves its effects in patients is unknown. In preliminary clinical models, pentosan polysulfate sodium adhered to the bladder wall mucosal membrane. The drug may act as a buffer to control cell permeability preventing irritating solutes in the urine from reaching the cells.

CLINICAL TRIALS

ELMIRON®was evaluated in two clinical trials for the relief of pain in patients with chronic interstitial cystitis (IC). All patients met the NIH definition of IC based upon the results of cystoscopy, cytology, and biopsy. One blinded, randomized, placebo-controlled study evaluated 151 patients (145 women, 5 men, 1 unknown) with a mean age of 44 years (range 18 to 81). Approximately equal numbers of patients received either placebo or ELMIRON®100 mg three times a day for 3 months. Clinical improvement in bladder pain was based upon the patient's own assessment. In this study, 28/74 (38%) of patients who received ELMIRON®and 13/74 (18%) of patients who received placebo showed greater than 50% improvement in bladder pain (p = 0.005).

A second clinical trial, the physician's usage study, was a prospectively designed retrospective analysis of 2499 patients who received ELMIRON®300 mg a day without blinding. Of the 2499 patients, 2220 were women, 254 were men, and 25 were of unknown sex. The patients had a mean age of 47 years and 23% were over 60 years of age. By 3 months, 1307 (52%) of the patients had dropped out or were ineligible for analysis; overall, 1192 (48%) received ELMIRON®for 3 months; 892 (36%) received ELMIRON®for 6 months; and 598 (24%) received ELMIRON®for one year.

Patients had unblinded evaluations every 3 months for the patient's rating of overall change in pain in comparison to baseline and for the difference calculated in "pain/discomfort" scores. At baseline, pain/discomfort scores for the original 2499 patients were severe or unbearable in 60%, moderate in 33% and mild or none in 7% of patients. The extent of the patients' pain improvement is shown in Table 1.

At 3 months, 722/2499 (29%) of the patients originally in the study had pain scores that improved by one or two categories. By 6 months, in the 892 patients who continued taking ELMIRON®, an additional 116/2499 (5%) of patients had improved pain scores. After 6 months, the percent of patients who reported the first onset of pain relief was less than 1.5% of patients who originally entered in the study (see Table 2).

Table 1: Pain Scores in Reference to Baseline in Open Label Physician's Usage Study (N=2499) [Trial not designed to detect onset of pain relief]
Efficacy Parameter | 3 months [CI = 95% confidence interval] | 6 months
Patient Rating of Overall Change in Pain (Recollection of difference between current pain and baseline pain) [6-point scale: 1 = worse, 2 = no better, 3 = slightly improved, 4 = moderately improved, 5 = greatly improved, 6 = symptom gone] | N=1161 Median = 3 Mean = 3.44 CI: (3.37, 3.51) | N=724 Median = 4 Mean = 3.91 CI: (3.83, 3.99)
Change in Pain/Discomfort Score (Calculated difference in scores at the time point and baseline) [3-point scale: 1 = none or mild, 2 = moderate, 3 = severe or unbearable] | N=1440 Median = 1 Mean = 0.51 CI: (0.45, 0.57) | N=904 Median = 1 Mean = 0.66 CI: (0.61, 0.71)

Table 2: Number (%) of Patients with New Relief of Pain/Discomfort [First-time Improvement in pain/discomfort score by 1 or 2 categories] in the Open-Label Physician's Usage Study (N=2499)
 | at 3 months [Number (%) of patients with improvement of pain/discomfort score at 3 months when compared to baseline] (n=1192) | at 6 months [Number (%) of patients without pain/discomfort improvement at 3 months who had improvement at 6 months] (n=892)
Considering only the patients who continued treatment | 722/1192 (61%) | 116/892 (13%)
Considering all the patients originally enrolled in the study | 722/2499 (29%) | 116/2499 (5%)

INDICATIONS AND USAGE

ELMIRON®(pentosan polysulfate sodium) is indicated for the relief of bladder pain or discomfort associated with interstitial cystitis.

CONTRAINDICATIONS

ELMIRON®is contraindicated in patients with known hypersensitivity to the drug, structurally related compounds, or excipients.

WARNINGS

Retinal Pigmentary Changes

Pigmentary changes in the retina, reported in the literature as pigmentary maculopathy, have been identified with long-term use of ELMIRON®(see ADVERSE REACTIONS). Although most of these cases occurred after 3 years of use or longer, cases have been seen with a shorter duration of use. While the etiology is unclear, cumulative dose appears to be a risk factor. Visual symptoms in the reported cases included difficulty reading, slow adjustment to low or reduced light environments, and blurred vision. The visual consequences of these pigmentary changes are not fully characterized. Caution should be used in patients with retinal pigment changes from other causes in which examination findings may confound the appropriate diagnosis, follow-up, and treatment. Detailed ophthalmologic history should be obtained in all patients prior to starting treatment with ELMIRON®. If there is a family history of hereditary pattern dystrophy, genetic testing should be considered. For patients with pre-existing ophthalmologic conditions, a comprehensive baseline retinal examination (including color fundoscopic photography, ocular coherence tomography (OCT), and auto-fluorescence imaging) is recommended prior to starting therapy. A baseline retinal examination (including OCT and auto-fluorescence imaging) is suggested for all patients within six months of initiating treatment and periodically while continuing treatment. If pigmentary changes in the retina develop, then risks and benefits of continuing treatment should be re-evaluated, since these changes may be irreversible. Follow-up retinal examinations should be continued given that retinal and vision changes may progress even after cessation of treatment.

PRECAUTIONS

General

ELMIRON®is a weak anticoagulant (1/15 the activity of heparin). At a daily dose of 300 mg (n=128), rectal hemorrhage was reported as an adverse event in 6.3% of patients. Bleeding complications of ecchymosis, epistaxis, and gum hemorrhage have been reported (see ADVERSE REACTIONS). Patients undergoing invasive procedures or having signs/symptoms of underlying coagulopathy or other increased risk of bleeding (due to other therapies such as coumarin anticoagulants, heparin, t-PA, streptokinase, high dose aspirin, or nonsteroidal anti-inflammatory drugs) should be evaluated for hemorrhage. Patients with diseases such as aneurysms, thrombocytopenia, hemophilia, gastrointestinal ulcerations, polyps, or diverticula should be carefully evaluated before starting ELMIRON®.

A similar product that was given subcutaneously, sublingually, or intramuscularly (and not initially metabolized by the liver) is associated with delayed immunoallergic thrombocytopenia with symptoms of thrombosis and hemorrhage. Caution should be exercised when using ELMIRON®in patients who have a history of heparin-induced thrombocytopenia.

Alopecia is associated with pentosan polysulfate and with heparin products. In clinical trials of ELMIRON®, alopecia began within the first 4 weeks of treatment. Ninety-seven percent (97%) of the cases of alopecia reported were alopecia areata, limited to a single area on the scalp.

Hepatic Insufficiency

ELMIRON®has not been studied in patients with hepatic insufficiency. Because there is evidence of hepatic contribution to the elimination of ELMIRON®, hepatic impairment may have an impact on the pharmacokinetics of ELMIRON®. Caution should be exercised when using ELMIRON®in this patient population.

Mildly (< 2.5 × normal) elevated transaminase, alkaline phosphatase, γ-glutamyl transpeptidase, and lactic dehydrogenase occurred in 1.2% of patients. The increases usually appeared 3 to 12 months after the start of ELMIRON®therapy, and were not associated with jaundice or other clinical signs or symptoms. These abnormalities are usually transient, may remain essentially unchanged, or may rarely progress with continued use. Increases in PTT and PT (< 1% for both) or thrombocytopenia (0.2%) were noted.

Information for Patients

Advise the patient to read the FDA-approved patient labeling (Medication Guide).

Patients should take the drug as prescribed, in the dosage prescribed, and no more frequently than prescribed.

Patients should be informed that changes in vision should be reported and evaluated. Retinal examinations including optical coherence tomography (OCT) and auto-fluorescence imaging are suggested for all patients within six months of starting ELMIRON®and periodically during long-term treatment (see WARNINGS).

Patients should be reminded that ELMIRON®has a weak anticoagulant effect. This effect may increase bleeding times.

Laboratory Test Findings

Pentosan polysulfate sodium did not affect prothrombin time (PT) or partial thromboplastin time (PTT) up to 1200 mg per day in 24 healthy male subjects treated for 8 days. Pentosan polysulfate sodium also inhibits the generation of factor Xa in plasma and inhibits thrombin-induced platelet aggregation in human platelet rich plasma ex vivo(see PRECAUTIONS-Hepatic Insufficiency).

Carcinogenicity, Mutagenesis, Impairment of Fertility

Long-term carcinogenicity studies of ELMIRON®in F344/N rats and B6C3F1 mice have been conducted. In these studies, ELMIRON®was orally administered once daily via gavage, 5 days per week, for up to 2 years. The dosages administered to mice were 56, 168 or 504 mg/kg. The dosages administered to rats were 14, 42, or 126 mg/kg for males, and 28, 84, or 252 mg/kg for females. The dosages tested were up to 60 times the maximum recommended human dose (MRHD) in rats, and up to 117 times the MRHD in mice, on a mg/kg basis. The results of these studies in rodents showed no clear evidence of drug-related tumorigenesis or carcinogenic risk.

Pentosan polysulfate sodium was not clastogenic or mutagenic when tested in the mouse micronucleus test or the Ames test (S. typhimurium). The effect of pentosan polysulfate sodium on spermatogenesis has not been investigated.

Pregnancy

Reproduction studies have been performed in mice and rats with intravenous daily doses of 15 mg/kg, and in rabbits with 7.5 mg/kg. These doses are 0.42 and 0.14 times the daily oral human doses of ELMIRON®when normalized to body surface area. These studies did not reveal evidence of impaired fertility or harm to the fetus from ELMIRON®. Direct in vitrobathing of cultured mouse embryos with pentosan polysulfate sodium (PPS) at a concentration of 1 mg/mL may cause reversible limb bud abnormalities. Adequate and well-controlled studies have not been performed in pregnant women. Because animal studies are not always predictive of human response, this drug should be used in pregnancy only if clearly needed.

Nursing Mothers

It is not known whether this drug is excreted in human milk. Because many drugs are excreted in human milk, caution should be exercised when ELMIRON®is administered to a nursing woman.

Pediatric Use

Safety and effectiveness in pediatric patients below the age of 16 years have not been established.

ADVERSE REACTIONS

ELMIRON®was evaluated in clinical trials in a total of 2627 patients (2343 women, 262 men, 22 unknown) with a mean age of 47 [range 18 to 88 with 581 (22%) over 60 years of age]. Of the 2627 patients, 128 patients were in a 3-month trial and the remaining 2499 patients were in a long-term, unblinded trial.

Deaths occurred in 6/2627 (0.2%) patients who received the drug over a period of 3 to 75 months. The deaths appear to be related to other concurrent illnesses or procedures, except in one patient for whom the cause was not known.

Serious adverse events occurred in 33/2627 (1.3%) patients. Two patients had severe abdominal pain or diarrhea and dehydration that required hospitalization. Because there was not a control group of patients with interstitial cystitis who were concurrently evaluated, it is difficult to determine which events are associated with ELMIRON®and which events are associated with concurrent illness, medicine, or other factors.

Adverse Experience in Placebo-Controlled Clinical Trials of ELMIRON®100 mg Three Times a Day for 3 Months
Body System/Adverse Experience | ELMIRON® n=128 | Placebo n=130
CNSOverall Number of Patients [Within a body system, the individual events do not sum to equal overall number of patients because a patient may have more than one event.] | 3 | 5
Insomnia | 1 | 0
Headache | 1 | 3
Severe Emotional Lability/Depression | 2 | 1
Nystagmus/Dizziness | 1 | 1
Hyperkinesia | 1 | 1
GIOverall Number of Patients | 7 | 7
Nausea | 3 | 3
Diarrhea | 3 | 6
Dyspepsia | 1 | 0
Jaundice | 0 | 1
Vomiting | 0 | 2
Skin/AllergicOverall Number of Patients | 2 | 4
Rash | 0 | 2
Pruritus | 0 | 2
Lacrimation | 1 | 1
Rhinitis | 1 | 1
Increased Sweating | 1 | 0
OtherOverall Number of Patients | 1 | 3
Amenorrhea | 0 | 1
Arthralgia | 0 | 1
Vaginitis | 1 | 1
Total Events | 17 | 27
Total Number of Patients Reporting Adverse Events | 13 | 19

The adverse events described below were reported in an unblinded clinical trial of 2499 interstitial cystitis patients treated with ELMIRON®. Of the original 2499 patients, 1192 (48%) received ELMIRON®for 3 months; 892 (36%) received ELMIRON®for 6 months; and 598 (24%) received ELMIRON®for one year, 355 (14%) received ELMIRON®for 2 years, and 145 (6%) for 4 years.

Frequency (1 to 4%): Alopecia (4%), diarrhea (4%), nausea (4%), headache (3%), rash (3%), dyspepsia (2%), abdominal pain (2%), liver function abnormalities (1%), dizziness (1%).

Frequency (≤ 1%):

Digestive:Vomiting, mouth ulcer, colitis, esophagitis, gastritis, flatulence, constipation, anorexia, gum hemorrhage.

Hematologic:Anemia, ecchymosis, increased prothrombin time, increased partial thromboplastin time, leukopenia, thrombocytopenia.

Hypersensitive Reactions:Allergic reaction, photosensitivity.

Respiratory System:Pharyngitis, rhinitis, epistaxis, dyspnea.

Skin and Appendages:Pruritus, urticaria.

Special Senses:Conjunctivitis, tinnitus, optic neuritis, amblyopia, retinal hemorrhage.

Post-Marketing Experience

The following adverse reactions have been identified during post approval use of pentosan polysulfate sodium; because these reactions were reported voluntarily from a population of uncertain size, it is not always possible to reliably estimate their frequency or establish a causal relationship to drug exposure:

- pigmentary changes in the retina (see WARNINGS).

Rectal Hemorrhage

ELMIRON®was evaluated in a randomized, double-blind, parallel group, Phase 4 study conducted in 380 patients with interstitial cystitis dosed for 32 weeks. At a daily dose of 300 mg (n=128), rectal hemorrhage was reported as an adverse event in 6.3% of patients. The severity of the events was described as "mild" in most patients. Patients in that study who were administered ELMIRON®900 mg daily, a dose higher than the approved dose, experienced a higher incidence of rectal hemorrhage, 15%.

Liver Function Abnormality

A randomized, double-blind, parallel group, Phase 2 study was conducted in 100 men (51 ELMIRON®and 49 placebo) dosed for 16 weeks. At a daily dose of 900 mg, a dose higher than the approved dose, elevated liver function tests were reported as an adverse event in 11.8% (n=6) of ELMIRON®-treated patients and 2% (n=1) of placebo-treated patients.

OVERDOSAGE

Overdose has not been reported. Based upon the pharmacodynamics of the drug, toxicity is likely to be reflected as anticoagulation, bleeding, thrombocytopenia, liver function abnormalities, and gastric distress (see CLINICAL PHARMACOLOGYand PRECAUTIONS). At a daily dose of 900 mg for 32 weeks (n=127) in a clinical trial, rectal hemorrhage was reported as an adverse event in 15% of patients. At a daily dose of ELMIRON®900 mg for 16 weeks in a clinical trial that enrolled 51 patients in the ELMIRON®group and 49 in the placebo group, elevated liver function tests were reported as an adverse event in 11.8% of patients in the ELMIRON®group and 2% of patients in the placebo group. In the event of acute overdosage, the patient should be given gastric lavage if possible, carefully observed and given symptomatic and supportive treatment.

DOSAGE AND ADMINISTRATION

The recommended dose of ELMIRON®is 300 mg/day taken as one 100 mg capsule orally three times daily. The capsules should be taken with water at least 1 hour before meals or 2 hours after meals.

Patients receiving ELMIRON®should be reassessed after 3 months. If improvement has not occurred and if limiting adverse events are not present, ELMIRON®may be continued for another 3 months.

The clinical value and risks of continued treatment in patients whose pain has not improved by 6 months is not known.

HOW SUPPLIED

ELMIRON®is supplied in white opaque hard gelatin capsules imprinted "BNP7600" containing 100 mg pentosan polysulfate sodium. Supplied in bottles of 100 capsules.

NDC NUMBER 50458-098-01

Storage

Store at 20 °C to 25 °C (68 °F to 77 °F); excursions permitted to 15 °C to 30 °C (59 °F to 86 °F).

Keep out of reach of children.

ELMIRON is a registered trademark of Teva Branded Pharmaceutical Products R&D Inc., used under license.

Product of Germany

Manufactured for:
Janssen Pharmaceuticals, Inc.
Titusville, New Jersey 08560, USA
For patent information: www.janssenpatents.com
© Johnson & Johnson and its affiliates 2002

Revised: 07/2024

MEDICATION GUIDE
ELMIRON®(EL ma ron)
(pentosan polysulfate sodium)
capsules, for oral use

What is the most important information I should know about ELMIRON?
Serious side effects have been reported with the use of ELMIRON, including:

- Changes in the retina of the eye (pigmentary maculopathy).Taking ELMIRON may be associated with pigment changes in the retina of the eye that may continue even after stopping treatment with ELMIRON. Tell your healthcare provider including your eye doctor right away if you have any vision changes including any of these symptoms:

- difficulty reading

- your vision takes longer to adjust to low or reduced light

- blurred vision

Throughout your treatment, regular eye examinations that include retinal examinations are suggested for early detection of retinal/macular changes. Your doctor will discuss with you when to get your first eye examination and follow-up exams, and whether the treatment should be continued.

- Increased bleeding.ELMIRON may increase bleeding. Tell your healthcare provider right away if you have any of these symptoms:

- bruising easily

- nosebleeds

- bleeding gums

- blood in your stool

Your risk of bleeding may be increased if you take ELMIRON along with other medicines such as:

- warfarin sodium
- heparin

- high doses of aspirin
- anti-inflammatory medicines such as ibuprofen

Tell your healthcare provider if you are taking any of these medicines.
Before you start taking ELMIRON, tell your healthcare provider if you are going to have surgery. Your healthcare provider may stop ELMIRON before you have surgery. Talk to your healthcare provider about when to stop taking ELMIRON and when to start taking it again.

What is ELMIRON?

- ELMIRON is a prescription medicine used to treat bladder pain or discomfort associated with interstitial cystitis.
- It is not known if ELMIRON is safe and effective in children under 16 years of age.

Do not take ELMIRON if you:

- are allergic to pentosan polysulfate sodium or any of the ingredients in ELMIRON. See the end of this Medication Guide for a complete list of ingredients in ELMIRON.

Before your take ELMIRON, tell your healthcare provider about all of your medical conditions, including if you:

- have a personal or family history of eye problems of the retina.
- have a history of aneurysms.
- have problems with easy bleeding (thrombocytopenia).
- have hemophilia.
- have gastrointestinal problems such as ulcerations, polyps, or diverticula.
- have liver problems
- are pregnant or plan to become pregnant. ELMIRON should be used during pregnancy only if clearly needed. Tell your healthcare provider if you become pregnant while taking ELMIRON. You and your healthcare provider should decide if you should continue to take ELMIRON.
- are breastfeeding or plan to breastfeed. It is not known if ELMIRON passes into your breastmilk. You and your healthcare provider should decide if you will take ELMIRON or breastfeed.

Tell your healthcare provider about all the medicines you take,including prescription and over-the-counter medicines, vitamins, and herbal supplements.
Know the medicines you take. Keep a list of them to show your healthcare provider and pharmacist when you get a new medicine.

How should I take ELMIRON?

- Take ELMIRON exactly as your healthcare provider tells you to take it.
- Take 1 capsule of ELMIRON by mouth 3 times a day with water at least 1 hour before meals or 2 hours after meals. Each capsule contains 100 mg of ELMIRON.
- If you take too much ELMIRON, call your healthcare provider right away or go to the nearest emergency room.

What are the possible side effects of ELMIRON?
Serious side effects have been reported with the use of ELMIRON, including:
Changes in the retina of the eye
Increased bleeding
(See " What is the most important information I should know about ELMIRON?")
The most common side effects of ELMIRON are:

- hair loss
- diarrhea
- nausea

- stomach pain
- upset stomach
- headache

- rash
- abnormal liver function tests
- dizziness

These are not all of the possible side effects of ELMIRON.
Call your doctor for medical advice about side effects. You may report side effects to FDA at 1-800-FDA-1088.

How should I store ELMIRON?

- Store ELMIRON at room temperature between 68 °F to 77 °F (20 °C to 25 °C).
- Keep ELMIRON and all medicines out of the reach of children.

General information about the safe and effective use of ELMIRON.
Medicines are sometimes prescribed for purposes other than those listed in a Medication Guide. Do not use ELMIRON for a condition for which it was not prescribed. Do not give ELMIRON to other people, even if they have the same symptoms you have. It may harm them. You can ask your pharmacist or healthcare provider for information about ELMIRON that is written for health professionals.

What are the ingredients in ELMIRON?
Active ingredient:pentosan polysulfate sodium
Inactive ingredients:microcrystalline cellulose, magnesium stearate, gelatin, pharmaceutical glaze (modified) in SD-45, synthetic black iron oxide, FD&C Blue No. 2 aluminum lake, FD&C Red No. 40 aluminum lake, FD&C Blue No. 1 aluminum lake, D&C Yellow No. 10 aluminum lake, n-butyl alcohol, propylene glycol, SDA-3A alcohol, and titanium dioxide.

ELMIRON is a registered trademark of Teva Branded Pharmaceutical Products R&D Inc., used under license.
Product of Germany
Manufactured for:
Janssen Pharmaceuticals, Inc.
Titusville, New Jersey 08560, USA
For more information, go to www.ORTHOELMIRON.com or call 1-800-526-7736.
For patent information: www.janssenpatents.com
©Johnson & Johnson and its affiliates 2002, 2021

This Medication Guide has been approved by the U.S. Food and Drug Administration Revised: 07/2024

PRINCIPAL DISPLAY PANEL - 100 mg Capsule Bottle Label

NDC 50458-098-01

ELMIRON®
(pentosan polysulfate sodium)

CAPSULES

100 mg

Attention: Dispense the enclosed
Medication Guide to each patient.

Each capsule contains 100 mg
pentosan polysulfate sodium.

Rx only

100 Capsules

janssen